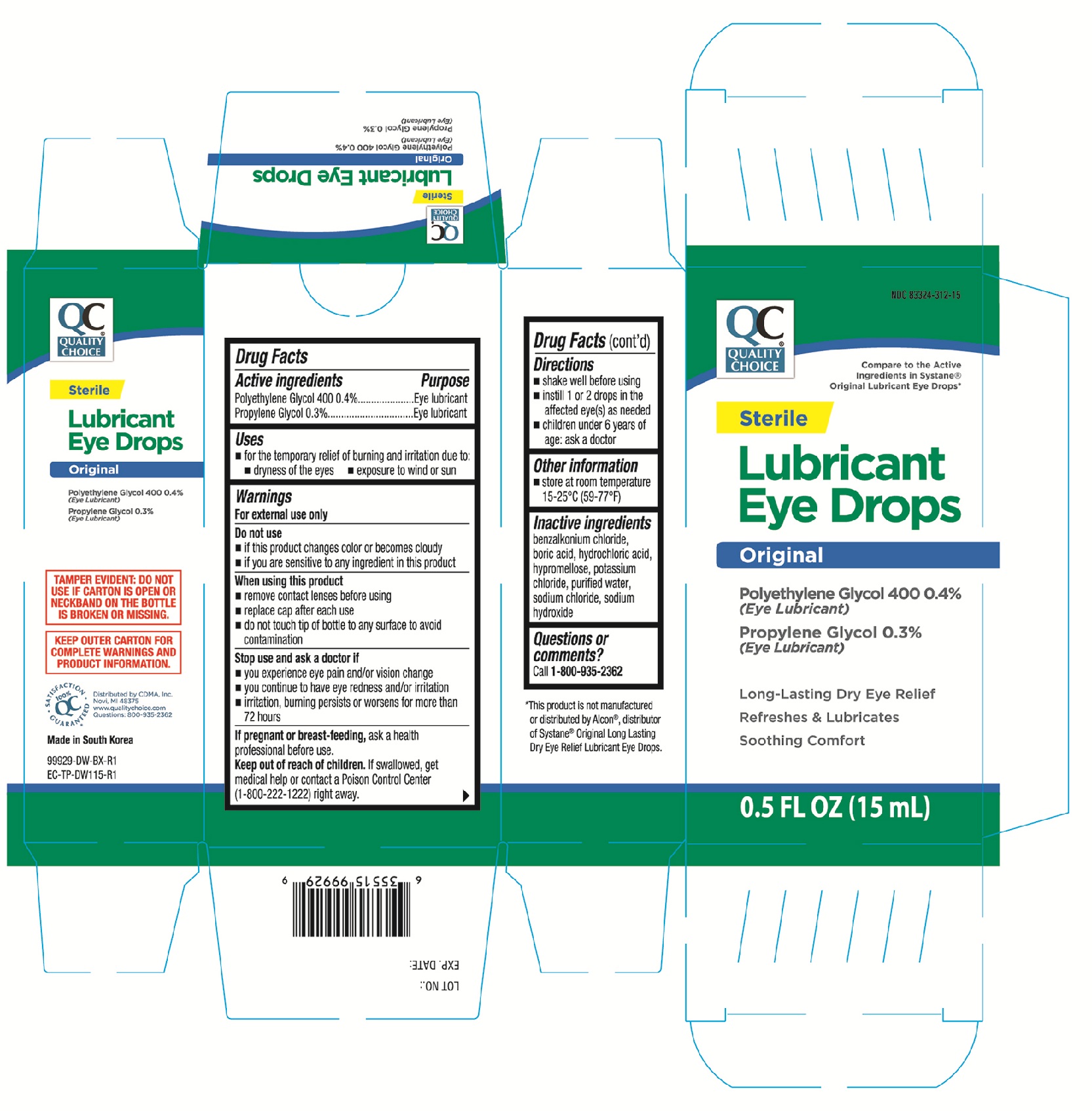 DRUG LABEL: Quality Choice
NDC: 83324-312 | Form: SOLUTION/ DROPS
Manufacturer: Chain Drug Marketing Association, Inc.
Category: otc | Type: HUMAN OTC DRUG LABEL
Date: 20251016

ACTIVE INGREDIENTS: POLYETHYLENE GLYCOL 400 4 mg/1 mL; PROPYLENE GLYCOL 3 mg/1 mL
INACTIVE INGREDIENTS: SODIUM HYDROXIDE; SODIUM CHLORIDE; BENZALKONIUM CHLORIDE; HYDROCHLORIC ACID; POTASSIUM CHLORIDE; BORIC ACID; HYPROMELLOSE, UNSPECIFIED; WATER

QC Original Lubricant Eye Drops 0.5fl.oz (NBE Systane Original) 99929 (Prop Gly)

Active ingredients Purpose

Polyethylene Glycol 400 0.4%.....................Eye lubricant

Propylene Glycol 0.3%................................Eye lubricant

Uses

- for the temporary relief of burning and irritation due to:
- dryness of the eyes
- exposure to wind or sun

Warnings

For external use only

Do not use

- if this product changes color or becomes cloudy
- if you are sensitive to any ingredient in this product

When using this product

- remove contact lenses before using
- replace cap after each use
- do not touch tip of bottle to any surface to avoid contamination

Stop use and ask a doctor if

- you experience eye pain and/or vision change
- you continue to have eye redness and/or irritation
- irritation, burning persists or worsens for more than 72 hours

PREGNANCY OR BREAST FEEDING

If pregnant or breast-feeding, ask a health professional before use.

Keep out of reach of children. If swallowed, get medical help or contact a Poison Control Center (1-800-222-1222) right away.

Directions

- shake well before using
- instill 1 or 2 drops in the affected eye(s) as needed
- children under 6 years of age: ask a dcotor

Other information

- store at room temperature 15-25°C (59-77°F)

Inactive ingredients

benzalkonium chloride, boric acid, hydrochloric acid, hypromellose, potassium chloride, purified water, sodium chloride, sodium hydroxide

DOSAGE AND ADMINISTRATION

Distributed by: CDMA, Inc.

Novi, MI 48375

Made in South Korea